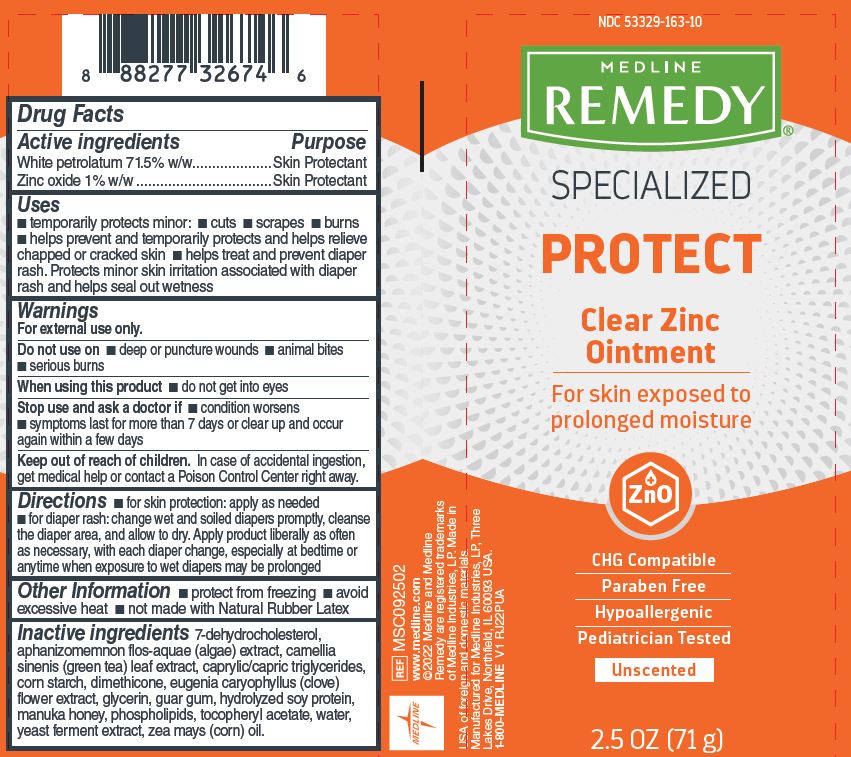 DRUG LABEL: Medline
NDC: 53329-163 | Form: OINTMENT
Manufacturer: Medline Industries, LP
Category: otc | Type: HUMAN OTC DRUG LABEL
Date: 20240129

ACTIVE INGREDIENTS: WHITE PETROLATUM 71.5 g/100 g; ZINC OXIDE 1 g/100 g
INACTIVE INGREDIENTS: ALPHA-TOCOPHEROL ACETATE; HYDROLYZED SOY PROTEIN (ENZYMATIC; 2000 MW); YEAST, UNSPECIFIED; HONEY; CORN OIL; LECITHIN, SOYBEAN; APHANIZOMENON FLOSAQUAE; 7-DEHYDROCHOLESTEROL; GLYCERIN; WATER; GREEN TEA LEAF; CLOVE; GUAR GUM; DIMETHICONE; STARCH, CORN; MEDIUM-CHAIN TRIGLYCERIDES

163 Remedy Specialized Clear Zinc Ointment

Active ingredients

White petrolatum 71.5% w/w

Zinc oxide 1% w/w

Purpose

Skin protectant

Uses

- temporarily protects minor:
- cuts
- scrapes
- burns
- helps prevent and temporarily protects and helps relieve chapped or cracked skin
- helps treat and prevent diaper rash. Protects minor skin irritation associated with diaper rash and helps seal out wetness

Warnings

For external use only.

Do not use on

- deep or puncture wounds
- animal bites
- serious burns

When using this product

- do not get into eyes

Stop use and ask a doctor if

- condition worsens
- symptoms last for more than 7 days or clear up and occur again within a few days

Keep out of reach of children.

In case of accidental ingestion, get medical help or contact a Poison Control Center right away.

Directions

- for skin protection: apply as needed
- for diaper rash: change wet and soiled diapers promptly, cleanse the diaper area, and allow to dry. Apply product liberally as often as necessary, with each diaper change, especially at bedtime or anytime when exposure to wet diapers may be prolonged

Other information

- protect from freezing
- avoid excessive heat
- not made with Natural Rubber Latex

Inactive ingredients

7-dehydrocholesterol, aphanizomemnon flos-aquae (algae) extract, camellia sinenis (green tea) leaf extract, caprylic/capric triglycerides, corn starch, dimethicone, eugenia caryophyllus (clove) flower extract, glycerin, guar gum, hydrolyzed soy protein, manuka honey, phospholipids, tocopheryl acetate, water, yeast ferment extract, zea mays (corn) oil.

Manufacturing Information

Manufactured for:
Medline Industries, LP

Three Lakes Drive, Northfield, IL 60093 USA

Made in USA of foreign and domestic materials

www.medline.com

1-800-MEDLINE (633-5453)

REF: MSC092502

V1 RJ22PUA